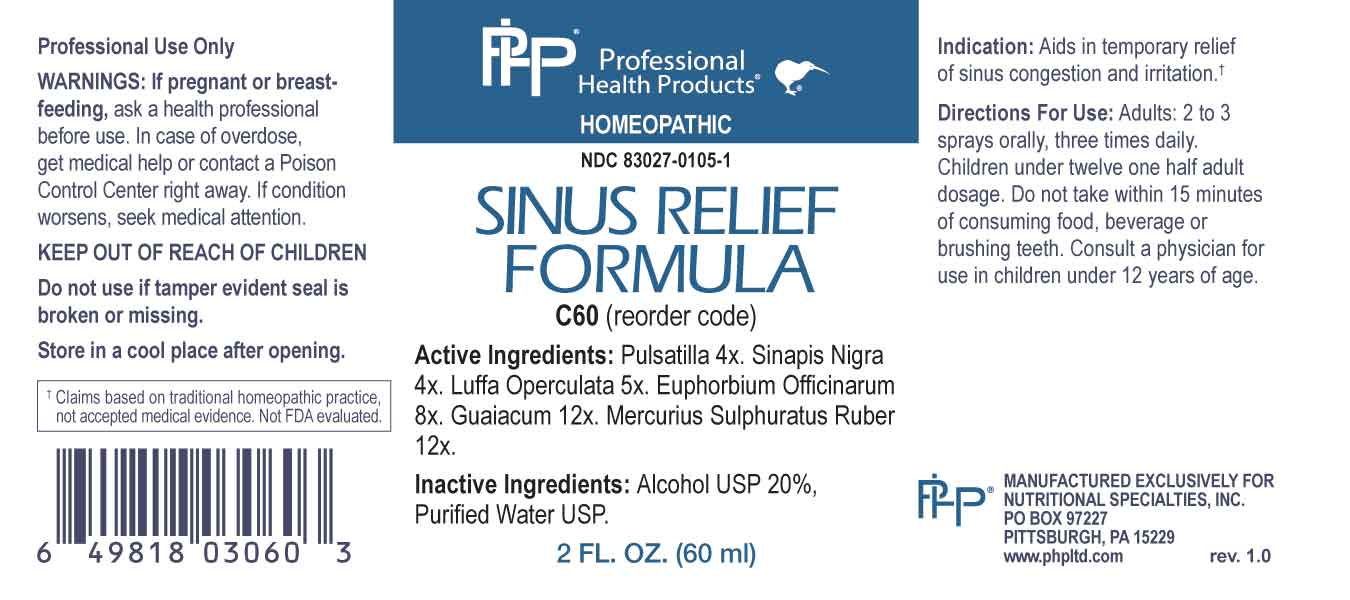 DRUG LABEL: Sinus Relief Formula
NDC: 83027-0105 | Form: SPRAY
Manufacturer: Nutritional Specialties, Inc.
Category: homeopathic | Type: HUMAN OTC DRUG LABEL
Date: 20230928

ACTIVE INGREDIENTS: PULSATILLA PRATENSIS WHOLE 4 [hp_X]/1 mL; BLACK MUSTARD SEED 4 [hp_X]/1 mL; LUFFA OPERCULATA FRUIT 5 [hp_X]/1 mL; EUPHORBIA RESINIFERA RESIN 8 [hp_X]/1 mL; GUAIACUM OFFICINALE RESIN 12 [hp_X]/1 mL; MERCURIC SULFIDE 12 [hp_X]/1 mL
INACTIVE INGREDIENTS: WATER; ALCOHOL

DRUG FACTS:

ACTIVE INGREDIENTS:

Pulsatilla 4X, Sinapis Nigra 4X, Luffa Operculata 5X, Euphorbium Officinarum 8X, Guaiacum 12X, Mercurius Sulphuratus Ruber 12X.

PURPOSE:

Aids in temporary relief of sinus congestion and irritation.†

†Claims based on traditional homeopathic practice, not accepted medical evidence. Not FDA evaluated.

WARNINGS:

Professional Use Only

If pregnant or breast-feeding, ask a health professional before use.

In case of overdose, get medical help or contact a Poison Control Center right away.

If condition worsens, seek medical attention.

KEEP OUT OF REACH OF CHILDREN

Do not use if tamper evident seal is broken or missing.

Store in a cool place after opening

KEEP OUT OF REACH OF CHILDREN:

In case of overdose, get medical help or contact a Poison Control Center right away.

DIRECTIONS:

Adults: 2 to 3 sprays orally, three times daily. Children under twelve one half adult dosage. Do not take within 15 minutes of consuming food, beverage or brushing teeth. Consult a physician for use in children under 12 years of age.

INDICATIONS:

Aids in temporary relief of sinus congestion and irritation.†

†Claims based on traditional homeopathic practice, not accepted medical evidence. Not FDA evaluated.

INACTIVE INGREDIENTS:

Alcohol USP 20%, Purified Water USP.

QUESTIONS:

MANUFACTURED EXCLUSIVELY FOR

NUTRITIONAL SPECIALTIES, INC.

PO BOX 97227

PITTSBURG, PA 15229

www.phpltd.com

PACKAGE LABEL DISPLAY:

Professional

Health Products

HOMEOPATHIC

NDC 83027-0105-1

SINUS RELIEF

FORMULA

2 FL. OZ (60 ml)